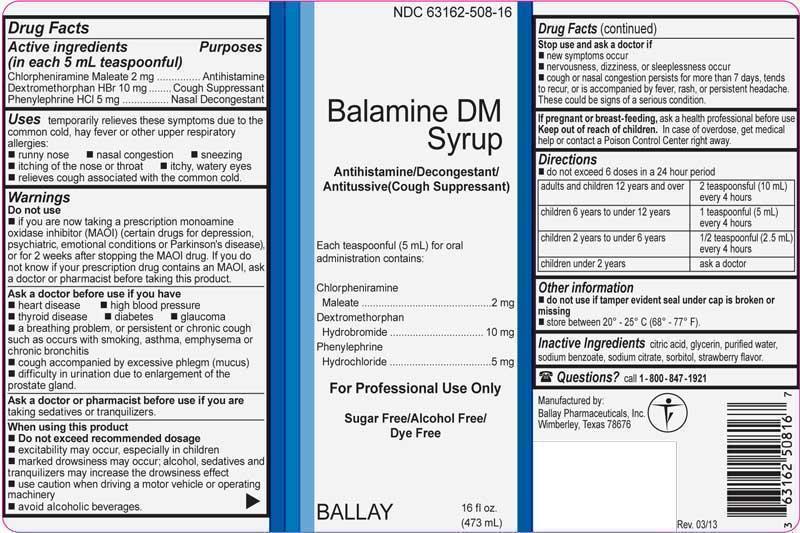 DRUG LABEL: Balamine
NDC: 63162-508 | Form: LIQUID
Manufacturer: Ballay Pharmaceuticals, Inc.
Category: otc | Type: HUMAN OTC DRUG LABEL
Date: 20131230

ACTIVE INGREDIENTS: CHLORPHENIRAMINE MALEATE 2 mg/5 mL; PHENYLEPHRINE HYDROCHLORIDE 5 mg/5 mL; DEXTROMETHORPHAN HYDROBROMIDE 10 mg/5 mL
INACTIVE INGREDIENTS: ANHYDROUS CITRIC ACID; GLYCERIN; WATER; SODIUM BENZOATE; SODIUM CITRATE; SORBITOL

Balamine DM Syrup

Active Ingredients (in each 5 mL teaspoonful)

Chlorpheniramine Maleate, USP 2 mg

Dextromethorphan HBr, USP 10 mg

Phenylephrine HCl, USP 5 mg

Purposes

Chlorpheniramine Maleate | Antihistamine
Dextromethorphan HBr | Cough Suppressant
Phenylephrine HCl | Nasal Decongestant

Uses

temporarily relieves these symptoms due to the common cold, hay fever or other upper respiratory allergies:

- runny nose
- nasal congestion
- sneezing
- itching of the nose or throat
- itchy, watery eyes
- relieves cough associated with the common cold

Warnings

Do not use

- if you are now taking a prescription monoamine oxidase inhibitor (MAOI) (certain drugs for depression, psychiatric, emotional conditions or Parkinson's disease), or for 2 weeks after stopping the MAOI drug. If you do not know if your prescription drug contains an MAOI, ask a doctor or pharmacist before taking this product.

Ask a doctor before use if you have

- heart disease
- high blood pressure
- thyroid disease
- diabetes
- glaucoma
- a breathing problem, or persistent or chronic cough such as occurs with smoking, asthma, emphysema or chronic bronchitis
- cough accompanied by excessive phlegm (mucus)
- difficulty in urination due to enlargement of the prostate gland.

Ask a doctor or pharmacist before use if you are

taking sedatives or tranquilizers.

When using this product

- Do not exceed recommended dosage
- excitability may occur, especially in children
- marked drowsiness may occur; alcohol, sedatives and tranquilizers may increase the drowsiness effect
- use caution when driving a motor vehicle or operating machinery
- avoid alcoholic beverages.

Stop use and ask a doctor if

- new symptoms occur
- nervousness, dizziness, or sleeplessness occur
- cough or nasal congestion persists for more than 7 days, tends to recur, or is accompanied by fever, rash, or persistent headache. These could be signs of a serious condition.

If pregnant or breast-feeding

ask a health professional before use.

Keep out of reach of children.

In case of overdose, get medical help or contact a Poison Control Center right away.

Directions

- do not exceed 6 doses in a 24 hour period

adults and children 12 years and over | 2 teaspoonsful (10 mL) every 4 hours
children 6 years to under 12 years | 1 teaspoonful (5 mL) every 4 hours
children 2 years to under 6 years | 1/2 teaspoonful (2.5 mL) every 4 hours
children under 2 years | ask a doctor

Other information

- do not use if tamper evident seal under cap is broken or missing
- store between 20° - 25° C (68° - 77° F).

Inactive Ingredients

citric acid, glycerin, purified water, sodium benzoate, sodium citrate, sorbitol, strawberry flavor.

Questions?

call 1-800-847-1921

Manufactured by:

Ballay Pharmaceuticals, Inc.

Wimberley, Texas 78676

PRINCIPAL DISPLAY PANEL - 473 mL Bottle Label

NDC 63162-508-16

Balamine DM

Syrup

Antihistamine/Decongestant/

Antitussive(Cough Suppressant)

Each teaspoonful (5 mL) for oral

administration contains:

Chlorpheniramine

Maleate .............................. 2 mg

Dextromethorphan

Hydrobromide ...................10 mg

Phenylephrine

Hydrochloride .....................5 mg

For Professional Use Only

Sugar Free/Alcohol Free/

Dye Free

BALLAY 16 fl oz.

(473 mL)